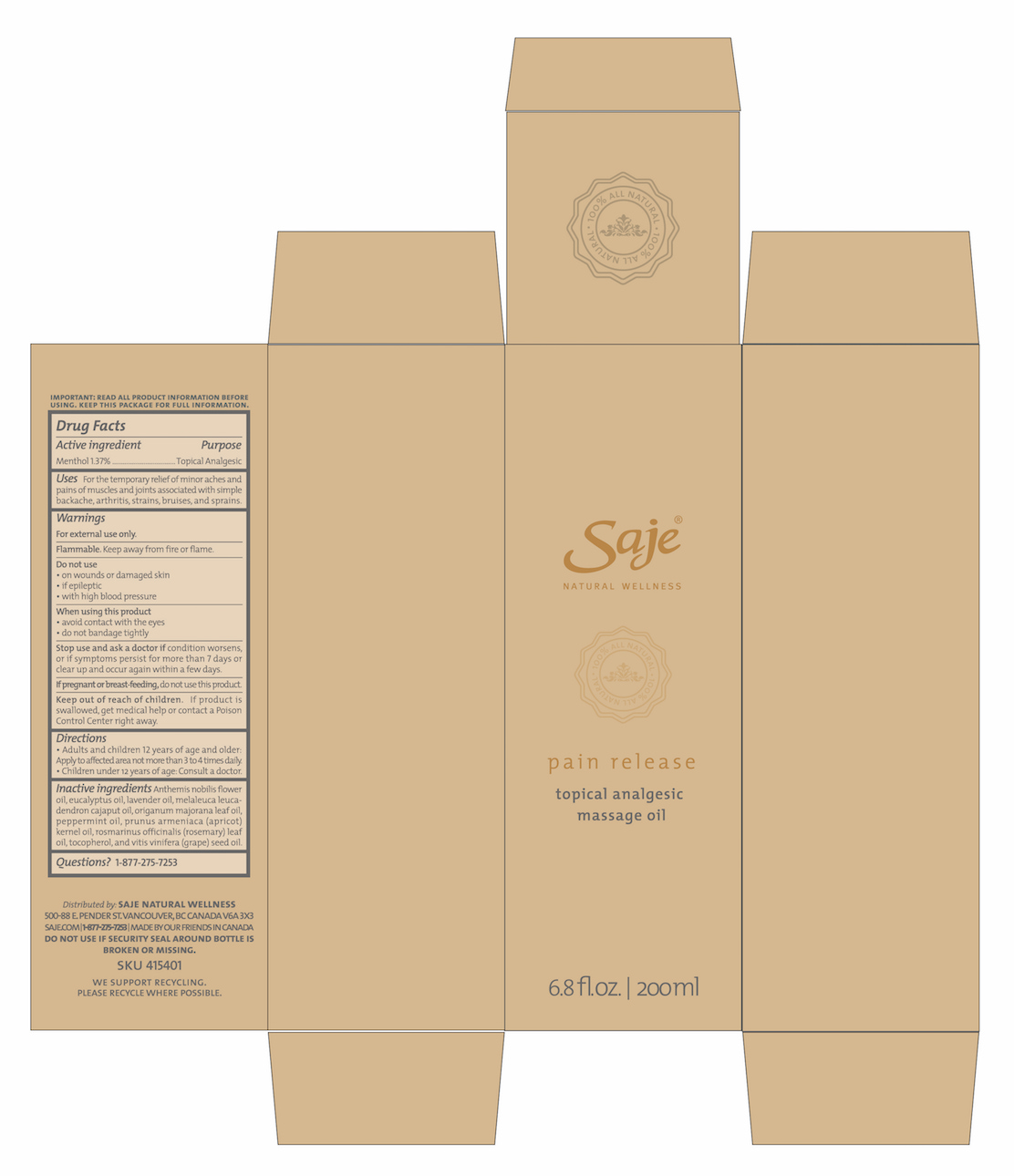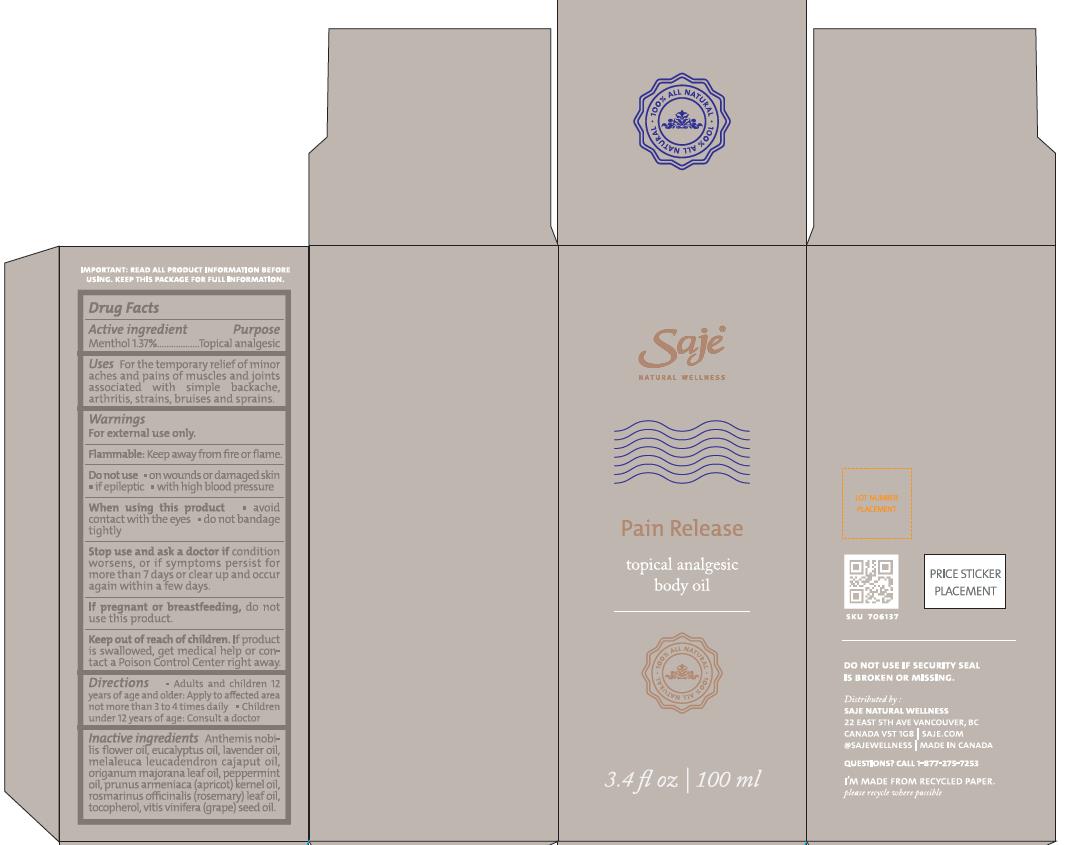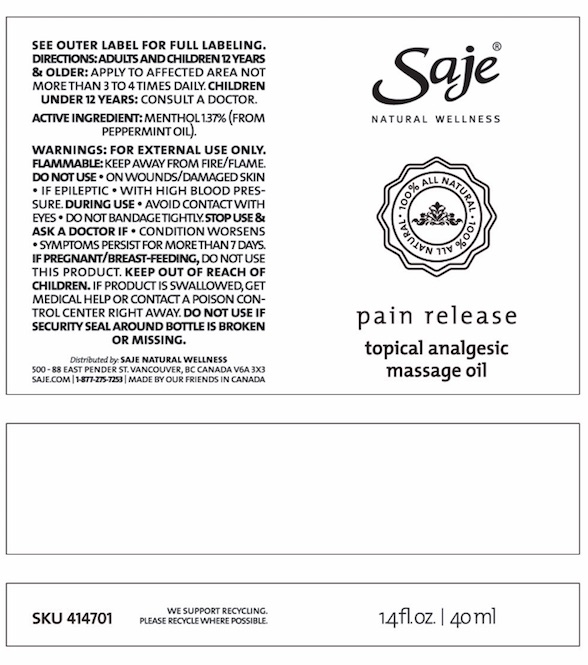 DRUG LABEL: Pain Release
NDC: 70983-007 | Form: OIL
Manufacturer: Saje Natural Business Inc.
Category: otc | Type: HUMAN OTC DRUG LABEL
Date: 20260113

ACTIVE INGREDIENTS: MENTHOL 12.18 mg/1 mL
INACTIVE INGREDIENTS: CHAMAEMELUM NOBILE FLOWER OIL; EUCALYPTUS OIL; LAVENDER OIL; CAJUPUT OIL; SWEET MARJORAM OIL; PEPPERMINT OIL; APRICOT KERNEL OIL; ROSEMARY OIL; TOCOPHEROL; GRAPE SEED OIL

Pain Release Topical Analgesic Massage Oil

DRUG FACTS Active ingredient

Menthol 1.37%

Purpose Topical Analgesic

Uses For temporary relief of minor aches and pains of muscles and joints associated with simple backache, arthritis, strains, brusies, and sprains.

Warnings

For external use only.

Flammable. Keep away from fire or flame

Do not use

- on wounds or damaged skin
- if epileptic
- with high blood pressure

When using this product

- avoid contact with the eyes.
- do not bandage tightly

Stop use and ask a doctor if

condition worsens, or if symptoms persist for more than 7 days or clear up and occur again within a few days.

If pregnant or breast-feeding,

do not use this product.

Keep out of reach of children.

If product is swallowed, get medical help or contact a Poison Control Center right away.

Directions

- Adults and children 12 years of age and older: Apply to affected area

DOSAGE AND ADMINISTRATION

not more than 3 to 4 times daily.

- Children under 12 years of age: consult a doctor.

Inactive ingredients

Anthemis nobilis flower oil, eucalyptus oil, lavender oil, melaleuca leucadendron cajaput oil, origanum majorana leaf oil, peppermint oil, prunus armeniaca (apricot) kernel oil, rosmarinus officinalis (rosemary) leaf oil, tocopherol, and vitis vinifera (grape) seed oil.

Questions?

1-877-275-7253

Distributed by: SAJE NATURAL WELLNESS 500-88 E. Pender St. Vancouver, BC Canada V6A 3X3 | saje.com | 1-877-275-7253 | Made by our friends in Canada

DO NOT USE IF SECURITY SEAL AROUND BOTTLE IS BROKEN OR MISSING.

SKU 415401

DISPOSAL AND WASTE HANDLING

We support recycling. Please recycle where possible.

Pain Release Topical Analgesic Massage Oil

Saje Natural Wellness

Pain Release

Topical Analgesic Massage Oil

1.4 fl.oz | 40ml

Saje Natural Wellness

Pain Release

Topical Analgesic Massage Oil

3.4 fl. oz. |100 ml

Saje Natural Wellness

Pain Release

Topical Analgesic Massage Oil

6.8 fl. oz. | 200 ml